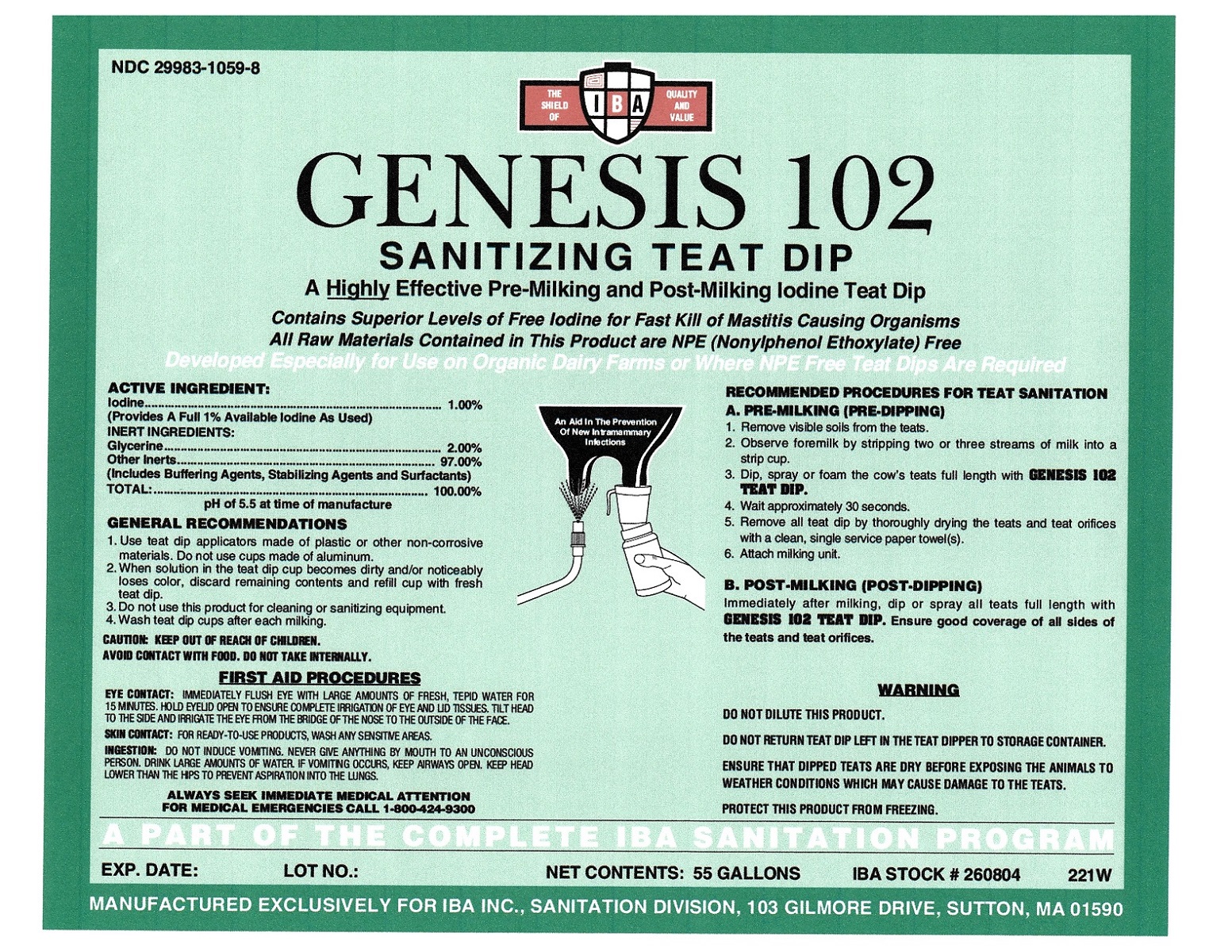 DRUG LABEL: Genesis 102
NDC: 29983-1059 | Form: LIQUID
Manufacturer: IBA
Category: animal | Type: OTC ANIMAL DRUG LABEL
Date: 20251126

ACTIVE INGREDIENTS: IODINE 1 kg/100 kg

Genesis 102

ACTIVE INGREDIENTS:

Iodine............................................................... 1.00%
(Provides A Full 1% Availabble Iodine As Used)

INERT INGREDIENTS:

Glycerine .......................................................... 2.00%
Other Inerts........... ......................................... 97.00%
TOTAL: ............................................................. 100.00%
pH of 5.5 at the time of manufacture

GENERAL RECOMMENDATIONS

1. Use teat dip applicators made of plastic or other non-corrosive materials. Do not use cups made of aluminum.
2. When solution in the teat dip cup becomes dirty and/or noticeably loses color, discard remaining contents and refill cup with fresh teat dip.
3. Do not use this product for cleaning or sanitizing equipment.
4. Wash teat dip cups after each milking.

Caution

KEEP OUT OF REACH OF CHILDREN.

Caution

AVOID CONTACT WITH FOOD. DO NOT TAKE INTERNALLY.

FIRST AID PROCEDURES

EYE CONTACT: IMMEDIATELY FLUSH EYE WITH LARGE AMOUNTS OF FRESH, TEPID WATER FOR 15 MINUTES. HOLD EYELID OPEN TO ENSURE COMPLETE IRRIGATION OF EYE AND LID TISSUES. TILT HEAD TO THE SIDE AND IRRIGATE THE EYE FROM THE BRIDGE OF THE NOSE TO THE OUTSIDE OF THE FACE.
SKIN CONTACT: FOR READY-TO-USE PRODUCTS, WASH ANY SENSITIVE AREAS.
INGESTION: DO NOT INDUCE VOMITING. NEVER GIVE ANYTHING BY MOUTH TO AN UNCONSCIOUS PERSON. DRINK LARGE AMOUNTS OF WATER. IF VOMITING OCCURS KEEP AIRWAYS OPEN. KEEP HEAD LOWER THAN THE HIPS TO PREVENT ASPIRATION INTO THE LUNGS.

ALWAYS SEEK IMMEDIATE MEDICAL ATTENTION

FOR MEDICAL EMERGENCIES CALL 1-800-424-9300

RECOMMENDED PROCEDURES FOR TEAT SANITATION:

A. PRE-MILKING (PRE-DIPPING)
1. Remove visible soils from the teats.
2. Observe formilk by stripping two or three streams of milk into a strip cup.
3. Dip or spray the cow's teats full length with Genesis 102 Teat Dip.
4. Wait approximately 30 seconds.
5. Remove all teat dip by thoroughly drying the teats and teat orifices with a clean, single service paper towels(s).
6. Attach milking unit.
B. POST-MILKING (POST-DIPPING)
1. Immediately after milking, dip or spray all teats full length with Genesis 102 Teat Dip. Ensure good coverage of all sides of the teats and teat orifices.

WARNINGS

DO NOT DILUTE THIS PRODUCT.DO NOT RETURN TEAT DIP LEFT IN THE TEAT DIPPER TO STORAGE CONTAINER.

ENSURE THAT DIPPED TEATS ARE DRY BEFORE EXPOSING THE ANIMALS TO WEATHER CONDITIONS WHICH MAY CAUSE DAMAGE TO THE TEATS.

PROTECT THIS PRODUCT FROM FREEZING.